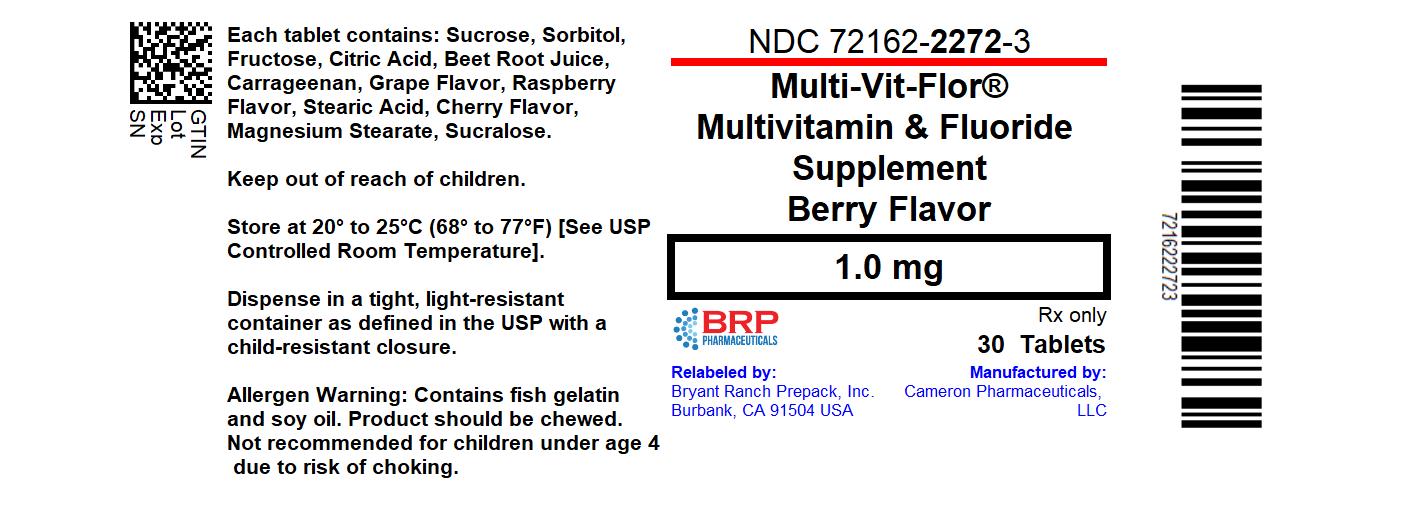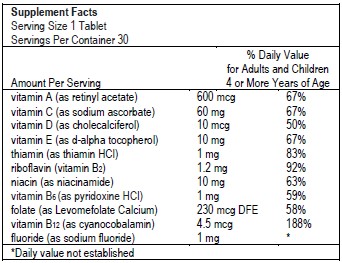 DRUG LABEL: Multi-Vit-Flor
NDC: 72162-2272 | Form: TABLET, CHEWABLE
Manufacturer: Bryant Ranch Prepack
Category: prescription | Type: HUMAN PRESCRIPTION DRUG LABEL
Date: 20240430

ACTIVE INGREDIENTS: SODIUM FLUORIDE 1 mg/1 1; VITAMIN A ACETATE 600 ug/1 1; SODIUM ASCORBATE 60 mg/1 1; CHOLECALCIFEROL 10 ug/1 1; .ALPHA.-TOCOPHEROL, D- 10 mg/1 1; THIAMINE HYDROCHLORIDE 1 mg/1 1; RIBOFLAVIN 1.2 mg/1 1; NIACINAMIDE 10 mg/1 1; PYRIDOXINE HYDROCHLORIDE 1 mg/1 1; LEVOMEFOLATE CALCIUM 230 ug/1 1; CYANOCOBALAMIN 4.5 ug/1 1
INACTIVE INGREDIENTS: SUCROSE; SORBITOL; FRUCTOSE; CITRIC ACID MONOHYDRATE; BEET JUICE; CARRAGEENAN; STEARIC ACID; MAGNESIUM STEARATE; SUCRALOSE

MULTI-VIT-FLOR
multivitamin and fluoride biphasic supplement tablet, chewable
Cameron Pharmaceuticals, LLC

Dispense by Prescription

DESCRIPTION

Multi-Vit-Flor

(Multivitamin with 0.25 mg, 0.5 mg and 1 mg of Fluoride) Chewable Tablet
Multivitamin and Fluoride Supplement

Supplement Facts
Serving Size 1 Tablet
Servings Per Container 30
Amount Per Serving |  |  |  | % Daily Value for Adults and Children 4 or More Years of Age
vitamin A (as retinyl acetate) | 600 mcg | 600 mcg | 600 mcg | 67%
vitamin C (as sodium ascorbate) | 60 mg | 60 mg | 60 mg | 67%
vitamin D (as cholecalciferol) | 10 mcg | 10 mcg | 10 mcg | 50%
vitamin E (as d-alpha-tocopherol) | 10 mg | 10 mg | 10 mg | 67%
thiamin (as thiamin HCl) | 1 mg | 1 mg | 1 mg | 83%
riboflavin (vitamin B2) | 1.2 mg | 1.2 mg | 1.2 mg | 92%
niacin (as niacinamide) | 10 mg | 10 mg | 10 mg | 63%
vitamin B6 (as pyridoxine HCl) | 1 mg | 1 mg | 1 mg | 59%
folate (as Levomefolate Calcium) | 230 mcg DFE | 230 mcg DFE | 230 mcg DFE | 58%
vitamin B12 (as cyanocobalamin) | 4.5 mcg | 4.5 mcg | 4.5 mcg | 188%
fluoride (as sodium fluoride) | 0.25 mg | 0.5 mg | 1 mg | [Daily value not established]

Ingredients: Sucrose, Sorbitol, Fructose, Citric Acid, Beet Root Juice, Carrageenan, Grape Flavor, Raspberry Flavor, Stearic Acid, Cherry Flavor, Magnesium Stearate, Sucralose.

Allergen Warning

Contains fish gelatin and soy oil.

Caution

This product should be chewed and is not recommended for children under age 4 due to risk of choking.

How Supplied

Multi-Vit-Flor® (Multivitamin with 1 mg of Fluoride) Chewable Tablet

MULTIVITAMIN & FLUORIDE
SUPPLEMENT

BERRY FLAVOR

NDC: 72162-2272-3: 30 Tablets in a BOTTLE

Repackaged/Relabeled by:

Bryant Ranch Prepack, Inc.

Burbank, CA 91504

Distributed by:
Cameron Pharmaceuticals, LLC
Louisville, KY

PACKAGE LABEL

Multi-Vit-Flor®(Multivitamin with 1 mg of Fluoride) Chewable Tablet

Extended Label